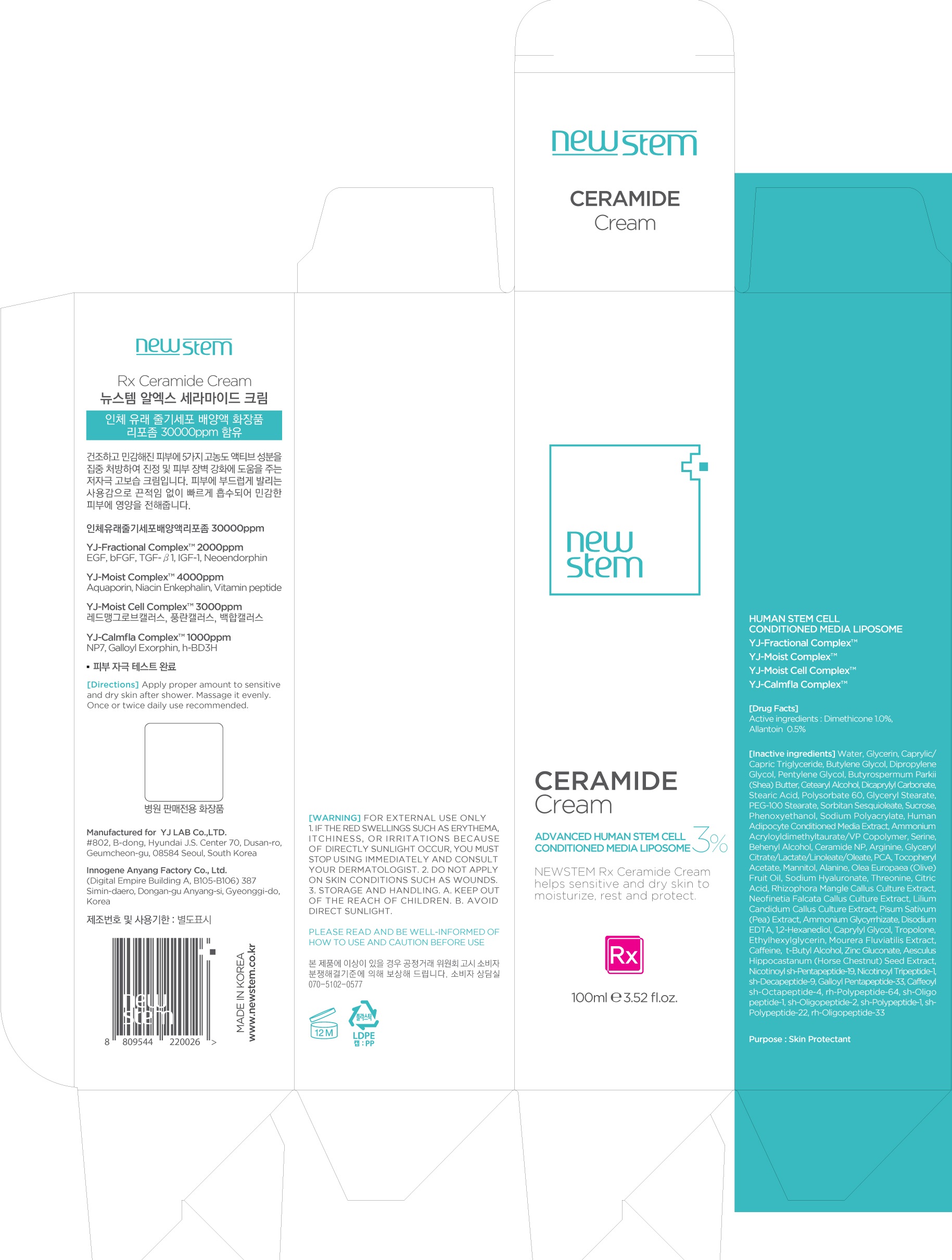 DRUG LABEL: NEWSTEM Rx Ceramide
NDC: 71759-010 | Form: CREAM
Manufacturer: Yj Lab Co., Ltd.
Category: otc | Type: HUMAN OTC DRUG LABEL
Date: 20200410

ACTIVE INGREDIENTS: Dimethicone 1.0 g/100 mL; Allantoin 0.5 g/100 mL
INACTIVE INGREDIENTS: Water; Glycerin

ACTIVE INGREDIENT

Active ingredients: Dimethicone 1.0%, Allantoin 0.5%

INACTIVE INGREDIENT

Inactive ingredients: Water, Glycerin, Caprylic/Capric Triglyceride, Butylene Glycol, Dipropylene Glycol, Pentylene Glycol, Butyrospermum Parkii (Shea) Butter, Cetearyl Alcohol, Dicaprylyl Carbonate, Stearic Acid, Polysorbate 60, Glyceryl Stearate, PEG-100 Stearate, Sorbitan Sesquioleate, Sucrose, Phenoxyethanol, Sodium Polyacrylate, Human Adipocyte Conditioned Media Extract, Ammonium Acryloyldimethyltaurate/VP Copolymer, Serine, Behenyl Alcohol, Ceramide NP, Arginine, Glyceryl Citrate/Lactate/Linoleate/Oleate, PCA, Tocopheryl Acetate, Mannitol, Alanine, Olea Europaea (Olive) Fruit Oil, Sodium Hyaluronate, Threonine, Citric Acid, Rhizophora Mangle Callus Culture Extract, Neofinetia Falcata Callus Culture Extract, Lilium Candidum Callus Culture Extract, Pisum Sativum (Pea) Extract, Ammonium Glycyrrhizate, Disodium EDTA, 1,2-Hexanediol, Caprylyl Glycol, Tropolone, Ethylhexylglycerin, Mourera Fluviatilis Extract, Caffeine, t-Butyl Alcohol, Zinc Gluconate, Aesculus Hippocastanum (Horse Chestnut) Seed Extract, Nicotinoyl sh-Pentapeptide-19, Nicotinoyl Tripeptide-1, sh-Decapeptide-9, Galloyl Pentapeptide-33, Caffeoyl sh-Octapeptide-4, rh-Polypeptide-64, sh-Oligopeptide-1, sh-Oligopeptide-2, sh-Polypeptide-1, sh-Polypeptide-22, rh-Oligopeptide-33

PURPOSE

Purpose: Skin Protectant

WARNINGS

Warnings: For external use only 1. If the Red swellings such as erythema, itchiness, or irritations because of directly sunlight occur, you must stop using immediately and Consult your dermatologist. 2. Do not apply on skin conditions such as wounds. 3. Storage and Handling. a. Keep out of the reach of children. b. Avoid direct sunlight.

KEEP OUT OF REACH OF CHILDREN

Uses

Uses: NEWSTEM Rx Ceramide Cream helps sensitive and dry skin to moisturize, rest and protect.

Directions

Directions: Apply proper amount to sensitive and dry skin after shower.Massage it evenly. Once or twice daily use recommended.